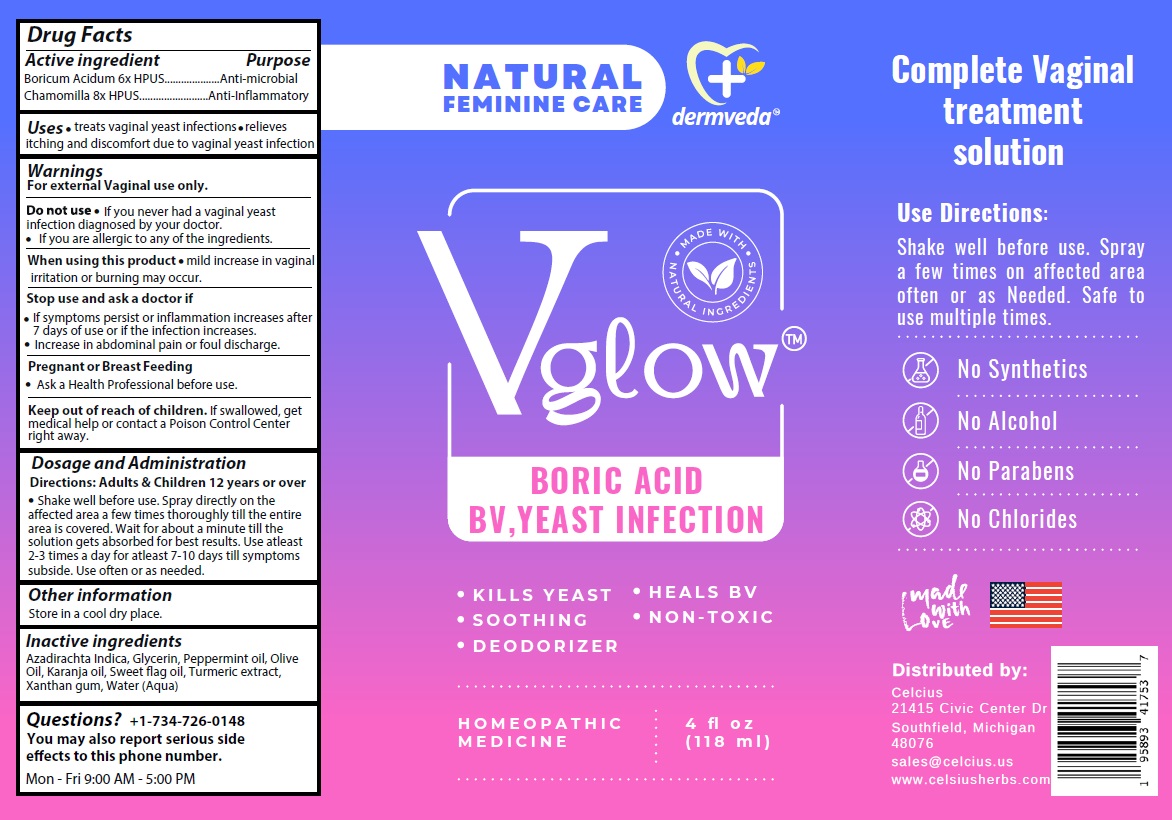 DRUG LABEL: dermveda BORIC ACID BV, YEAST INFECTION
NDC: 83819-102 | Form: SPRAY
Manufacturer: Celcius Corp.
Category: homeopathic | Type: HUMAN OTC DRUG LABEL
Date: 20260206

ACTIVE INGREDIENTS: BORIC ACID 6 [hp_X]/118 mL; CHAMOMILE 8 [hp_X]/118 mL
INACTIVE INGREDIENTS: AZADIRACHTA INDICA SEED OIL; GLYCERIN; PEPPERMINT OIL; OLIVE OIL; KARUM SEED OIL; CALAMUS OIL; TURMERIC; XANTHAN GUM; WATER

dermveda™ Vglow™ BORIC ACID BV, YEAST INFECTION

Active ingredient

Boricum Acidum 6x HPUS

Chamomilla 8x HPUS

Purpose

Anti-microbial

Anti-Inflammatory

Uses

• treats vaginal yeast infections • relieves itching and discomfort due to vaginal yeast infection

Warnings

For external Vaginal use only.

Do not use • If you never had a vaginal yeast infection diagnosed by your doctor.
• If you are allergic to any of the ingredients.

When using this product • mild increase in vaginal irritation or burning may occur.

Stop use and ask a doctor if
• If symptoms persist or inflammation increases after 7 days of use or if the infection increases.
• Increase in abdominal pain or foul discharge.

Pregnant or Breast Feeding
• Ask a Health Professional before use.

Keep out of reach of children. If swallowed, get medical help or contact a Poison Control Center right away.

Dosage and Administration

Directions: Adults & Children 12 years or over

• Shake well before use. Spray directly on the affected area a few times thoroughly till the entire area is covered. Wait for about a minute till the solution gets absorbed for best results. Use atleast 2-3 times a day for atleast 7-10 days till symptoms subside. Use often or as needed.

Other information

Store in a cool dry place.

Inactive ingredients

Azadirachta Indica, Glycerin, Peppermint oil, Olive Oil, Karanja oil, Sweet flag oil, Turmeric extract, Xanthan gum, Water (Aqua)

Questions?

+1-734-726-0148
You may also report serious side effects to this phone number.
Mon - Fri 9:00 AM -5:00 PM

NATURAL FEMININE CARE

MADE WITH NATURAL INGREDIENTS

- KILLS YEAST
- SOOTHING
- DEODORIZER
- HEALS BV
- NON-TOXIC

HOMEOPATHIC MEDICINE

Complete Vaginal treatment solution

No Synthetics
No Alcohol
No Parabens
No Chlorides

made with Love

Distributed by:
Celcius
21415 Civic Center Dr
Southfield, Michigan
48076
sales@celcius.us
www.celsiusherbs.com